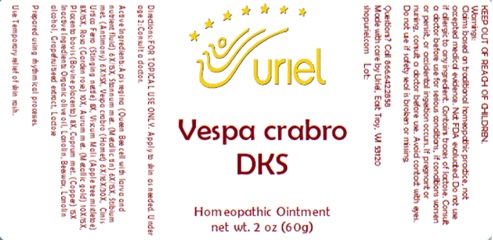 DRUG LABEL: Vespa Crabro DKS
NDC: 48951-9370 | Form: OINTMENT
Manufacturer: Uriel Pharmacy Inc.
Category: homeopathic | Type: HUMAN OTC DRUG LABEL
Date: 20241115

ACTIVE INGREDIENTS: VISCUM ALBUM FRUITING TOP 8 [hp_X]/1 g; ROYAL JELLY 6 [hp_X]/1 g; ANTIMONY 6 [hp_X]/1 g; COPPER 15 [hp_X]/1 g; URTICA DIOICA 8 [hp_X]/1 g; SEDUM ROSEUM WHOLE 10 [hp_X]/1 g; GOLD 10 [hp_X]/1 g; BOS TAURUS PLACENTA 8 [hp_X]/1 g; TIN 6 [hp_X]/1 g; VESPA CRABRO 6 [hp_X]/1 g
INACTIVE INGREDIENTS: LANOLIN ALCOHOLS; OLIVE OIL; LANOLIN; YELLOW WAX; CITRUS PARADISI SEED; LACTOSE, UNSPECIFIED FORM

Vespa crabro DKS

INDICATIONS AND USAGE

Directions: FOR TOPICAL USE ONLY.

DOSAGE AND ADMINISTRATION

Apply to skin as needed. Under age 2: Consult a doctor.

ACTIVE INGREDIENT

Active Ingredients: Apis regina (Queen Bee cell with larva and nutrient fluid) 6X/15X, Stannum met. (Metallic tin) 6X/15X, Stibium met. (Antimony) 6X/15X,Vespa crabro (Hornet) 6X/16X/30X, Cinis Urtica dioicae (Stinging nettle ash) 8X, Viscum Mali (Apple tree mistletoe) 8X/15X, Rosa (Garden rose) 10X, Aurum met. (Metallic gold) 10X/15X, Placenta bovis (Bovine placenta) 8X, Cuprum met. (Copper) 15X

INACTIVE INGREDIENT

Inactive Ingredients: Organic olive oil, Lanolin, Beeswax, Lanolin alcohol, Grapefruit seed extract, Lactose

Prepared using rhythmical processes.

PURPOSE

Use: Temporary relief of skin rash.

KEEP OUT OF REACH OF CHILDREN.

Warnings: FOR EXTERNAL USE ONLY.
Claims based on traditional homeopathic practice, not accepted medical evidence. Not FDA evaluated. Do not use if allergic to any ingredient. Consult a doctor before use for serious conditions, if conditions worsen or persist, or accidental ingestion occurs. Contains traces of lactose. If pregnant or nursing, consult a doctor before use. Avoid contact with eyes. Do not use if safety seal is broken or missing.

Questions? Call 866.642.2858
Made with care by Uriel, East Troy, WI 53120
shopuriel.com Lot: